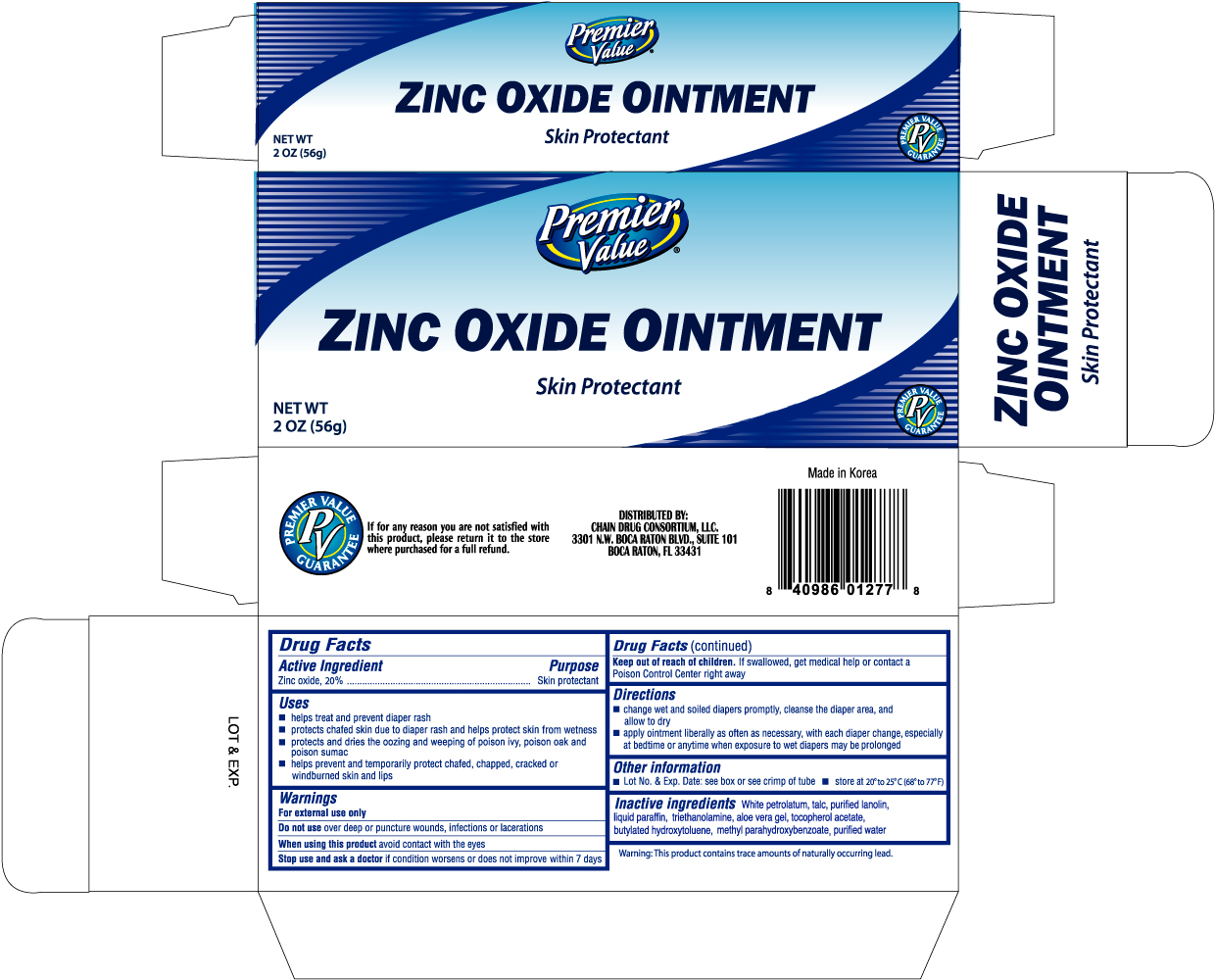 DRUG LABEL: PREMIER VALUE ZINC OXIDE
NDC: 68169-0130 | Form: OINTMENT
Manufacturer: TAI GUK PHARM. CO., LTD.
Category: otc | Type: HUMAN OTC DRUG LABEL
Date: 20101108

ACTIVE INGREDIENTS: ZINC OXIDE 20 g/100 g
INACTIVE INGREDIENTS: PETROLATUM; TALC; LANOLIN; MINERAL OIL; TROLAMINE; ALOE VERA LEAF; WATER

Drug Facts

Active Ingredient Purpose

Zinc oxide, 20% ..............................................................................Skin protectant

Uses

- helps treat and prevent diaper rash
- protects chafed skin due to diaper rash and helps protect skin from wetness
- protects and dries the oozing and weeping of poison ivy, poison oak and poison sumac
- helps prevent and temporarily protect chafed, chapped, cracked or windburned skin and lips

Warnings

For external use only

Do not use over deep or puncture wounds, infections or lacerations

When using this product avoid contact with the eyes

Stop use and ask a doctor if condition worsens or does not improve within 7 days

Keep out of reach of children. If swallowed, get medical help or contact a Poison Control Center right away.

Directions

- change wet and soiled diapers promptly, cleanse the diaper area, and allow to dry
- apply ointment liberally as often as necessary, with each diaper change, especially at bedtime or anytime when exposure to wet diapers may be prolonged

Other information

- Lot No. and Exp. Date: see box or see crimp of tube
- store at 20o to 25oC (68o to 77oF)

Inactive ingredients

White petrolatum, talc, purified lanolin, liquid paraffin, triethanolamine, aloe vera gel, tocopherol acetate, butylated hydroxyloluene, methyl parahydroxybenzoate, purified water

DOSAGE AND ADMINISTRATION

Distributed By:

Chain Drug Consortium, LLC.

3301 N.W. Boca Raton Blvd., Suite 101

Boca Raton, FL 33431

PACKAGE LABEL

Enter section text here